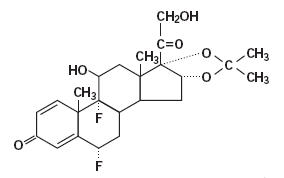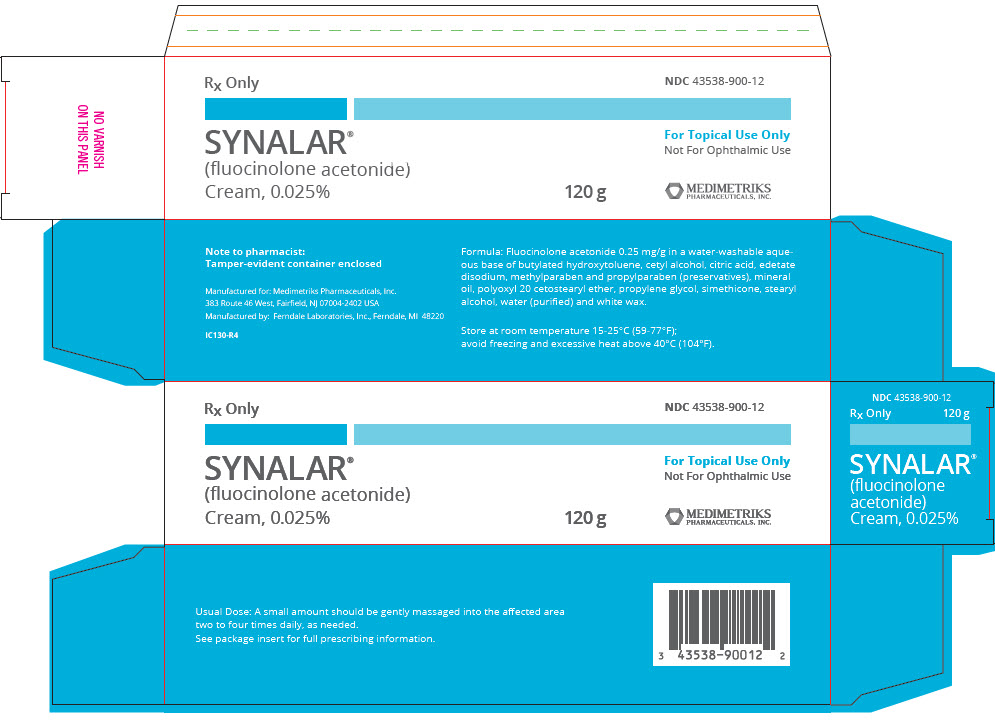 DRUG LABEL: Synalar
NDC: 43538-900 | Form: CREAM
Manufacturer: Medimetriks Pharmaceuticals, Inc.
Category: prescription | Type: HUMAN PRESCRIPTION DRUG LABEL
Date: 20240718

ACTIVE INGREDIENTS: fluocinolone acetonide 0.25 mg/1 g
INACTIVE INGREDIENTS: butylated hydroxytoluene; cetyl alcohol; anhydrous citric acid; edetate disodium; methylparaben; propylparaben; mineral oil; polyoxyl 20 cetostearyl ether; propylene glycol; dimethicone 350; silicon dioxide; stearyl alcohol; water; white wax

SYNALAR®
(fluocinolone acetonide)
Cream, 0.025%

for initiation of therapy in inflammatory dermatoses.
Rx Only

DESCRIPTION

SYNALAR® (fluocinolone acetonide) Cream 0.025% is intended for topical administration. The active component is the corticosteroid fluocinolone acetonide, which has the chemical name pregna-1,4-diene-3,20-dione,6,9-difluoro-11,21-dihydroxy-16,17-[(1-methylethylidene)bis (oxy)]-,(6α,11β,16α)-. It has the following chemical structure:

SYNALAR® Cream contains fluocinolone acetonide 0.25 mg/g in a water-washable aqueous base of butylated hydroxytoluene, cetyl alcohol, citric acid, edetate disodium, methylparaben and propylparaben (preservatives), mineral oil, polyoxyl 20 cetostearyl ether, propylene glycol, simethicone, stearyl alcohol, water (purified) and white beeswax.

CLINICAL PHARMACOLOGY

Topical corticosteroids share anti-inflammatory, anti-pruritic and vasoconstrictive actions.

MECHANISM OF ACTION

The mechanism of anti-inflammatory activity of the topical corticosteroids is unclear. Various laboratory methods, including vasoconstrictor assays, are used to compare and predict potencies and/or clinical efficacies of the topical corticosteroids. There is some evidence to suggest that a recognizable correlation exists between vasoconstrictor potency and therapeutic efficacy in man.

Pharmacokinetics

The extent of percutaneous absorption of topical corticosteroids is determined by many factors including the vehicle, the integrity of the epidermal barrier, and the use of occlusive dressings.

Topical corticosteroids can be absorbed from normal intact skin. Inflammation and/or other disease processes in the skin increase percutaneous absorption. Occlusive dressings substantially increase the percutaneous absorption of topical corticosteroids. Thus, occlusive dressings may be a valuable therapeutic adjunct for treatment of resistant dermatoses (see DOSAGE AND ADMINISTRATION).

Once absorbed through the skin, topical corticosteroids are handled through pharmacokinetic pathways similar to systemically administered corticosteroids. Corticosteroids are bound to plasma proteins in varying degrees. Corticosteroids are metabolized primarily in the liver and are then excreted by the kidneys. Some of the topical corticosteroids and their metabolites are also excreted into the bile.

INDICATIONS AND USAGE

SYNALAR® Cream is indicated for the relief of the inflammatory and pruritic manifestations of corticosteriod-responsive dermatoses.

CONTRAINDICATIONS

Topical corticosteroids are contraindicated in those patients with a history of hypersensitivity to any of the components of the preparation.

PRECAUTIONS

General

Systemic absorption of topical corticosteroids has produced reversible hypothalamic-pituitary-adrenal (HPA) axis suppression, manifestations of Cushing's syndrome, hyperglycemia, and glucosuria in some patients.

Conditions which augment systemic absorption include the application of the more potent steroids, use over large surface areas, prolonged use, and the addition of occlusive dressings.

Therefore, patients receiving a large dose of a potent topical steroid applied to a large surface area or under an occlusive dressing should be evaluated periodically for evidence of HPA axis suppression by using the urinary free cortisol and ACTH stimulation tests. If HPA axis suppression is noted, an attempt should be made to withdraw the drug, to reduce the frequency of application, or to substitute a less potent steroid.

Recovery of HPA axis function is generally prompt and complete upon discontinuation of the drug. Infrequently, signs and symptoms of steroid withdrawal may occur, requiring supplemental systemic corticosteroids.

Children may absorb proportionally larger amounts of topical corticosteroids and thus be more susceptible to systemic toxicity (see PRECAUTIONS—Pediatric Use).

If irritation develops, topical corticosteroids should be discontinued and appropriate therapy instituted.

As with any topical corticosteroid product, prolonged use may produce atrophy of the skin and subcutaneous tissues. When used on intertriginous or flexor areas, or on the face, this may occur even with short-term use.

In the presence of dermatological infections, the use of an appropriate antifungal or antibacterial agent should be instituted. If a favorable response does not occur promptly, the corticosteroid should be discontinued until the infection has been adequately controlled.

Information for the Patient

Patients using topical corticosteroids should receive the following information and instructions:

1. This medication is to be used as directed by the physician. It is for external use only. Avoid contact with the eyes.
2. Patients should be advised not to use this medication for any disorder other than that for which it was prescribed.
3. The treated skin area should not be bandaged or otherwise covered or wrapped as to be occlusive unless directed by the physician.
4. Patients should report any signs of local adverse reactions, especially under occlusive dressing.
5. Parents of pediatric patients should be advised not to use tight-fitting diapers or plastic pants on a child being treated in the diaper area, as these garments may constitute occlusive dressings.

Laboratory Tests

The following tests may be helpful in evaluating the HPA axis suppression:

Urinary free cortisol test
ACTH stimulation test

Carcinogenesis, Mutagenesis, and Impairment of Fertility

Long-term animal studies have not been performed to evaluate the carcinogenic potential or the effect on fertility of topical corticosteroids.

Studies to determine mutagenicity with prednisolone and hydrocortisone have revealed negative results.

Pregnancy Category C

Corticosteroids are generally teratogenic in laboratory animals when administered systemically at relatively low dosage levels. The more potent corticosteroids have been shown to be teratogenic after dermal application in laboratory animals. There are no adequate and well-controlled studies in pregnant women on teratogenic effects from topically applied corticosteroids. Therefore, topical corticosteroids should be used during pregnancy only if the potential benefit justifies the potential risk to the fetus. Drugs of this class should not be used extensively on pregnant patients, in large amounts, or for prolonged periods of time.

Nursing Mothers

It is not known whether topical administration of corticosteroids could result in sufficient systemic absorption to produce detectable quantities in breast milk. Systemically administered corticosteroids are secreted into breast milk in quantities not likely to have a deleterious effect on the infant. Nevertheless, caution should be exercised when topical corticosteroids are administered to a nursing woman.

Pediatric Use

Pediatric patients may demonstrate greater susceptibility to topical corticosteroidinduced hypothalmic-pituitary-adrenal (HPA) axis suppression and Cushing's syndrome than mature patients because of a larger skin surface area to body weight ratio.

HPA axis suppression, Cushing's syndrome, and intracranial hypertension have been reported in children receiving topical corticosteroids. Manifestations of adrenal suppression in children include linear growth retardation, delayed weight gain, low plasma cortisol levels, and absence of response to ACTH stimulation. Manifestations of intracranial hypertension include bulging fontanelles, headaches, and bilateral papilledema.

Administration of topical corticosteroids to children should be limited to the least amount compatible with an effective therapeutic regimen. Chronic corticosteroid therapy may interfere with the growth and development of children.

ADVERSE REACTIONS

The following local adverse reactions are reported infrequently with topical corticosteroids, but may occur more frequently with the use of occlusive dressings. These reactions are listed in an approximate decreasing order of occurrence:

Burning | Hypertrichosis | Maceration of the skin
Itching | Acneiform eruptions | Secondary infection
Irritation | Hypopigmentation | Skin atrophy
Dryness | Perioral dermatitis | Striae
Folliculitis | Allergic contact dermatitis | Miliaria

OVERDOSAGE

Topically applied corticosteroids can be absorbed in sufficient amounts to produce systemic effects (see PRECAUTIONS).

DOSAGE AND ADMINISTRATION

SYNALAR® Cream is generally applied to the affected area as a thin film from two to four times daily depending on the severity of the condition. In hairy sites, the hair should be parted to allow direct contact with the lesion.

Occlusive dressing may be used for the management of psoriasis or recalcitrant conditions. Some plastic films may be flammable and due care should be exercised in their use. Similarly, caution should be employed when such films are used on children or left in their proximity, to avoid the possibility of accidental suffocation.

If an infection develops, the use of the occlusive dressings should be discontinued and appropriate antimicrobial therapy instituted.

HOW SUPPLIED

SYNALAR® (fluocinolone acetonide) Cream 0.025% is supplied in

120 g Tube – NDC 43538-900-12

STORAGE

Store at room temperature 15-25°C (59-77°F); avoid freezing and excessive heat above 40°C (104°F).

To report SUSPECTED ADVERSE REACTIONS, contact Medimetriks Pharmaceuticals, Inc. at 1-973-882-7512 or FDA at 1-800-FDA-1088 or www.fda/gov/medwatch.

Manufactured for:

MEDIMETRIKS
PHARMACEUTICALS, INC.

383 Route 46 West, Fairfield, NJ 07004-2402 USA
www.medimetriks.com

Manufactured by: Ferndale Laboratories, Inc., Ferndale, MI 48220

IP027-R3
Rev. 10/2022

PRINCIPAL DISPLAY PANEL - 120 g Tube Carton

Rx Only

NDC 43538-900-12

SYNALAR®
(fluocinolone acetonide)
Cream, 0.025%

For Topical Use Only
Not For Ophthalmic Use

120 g

MEDIMETRIKS
PHARMACEUTICALS, INC.